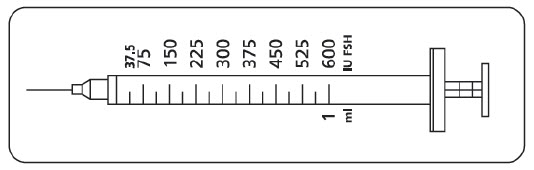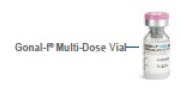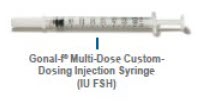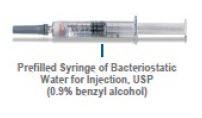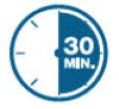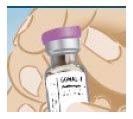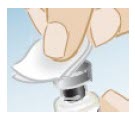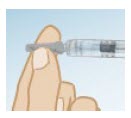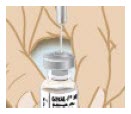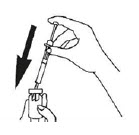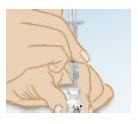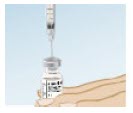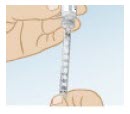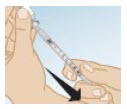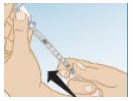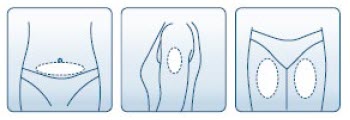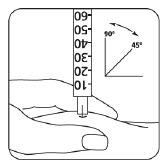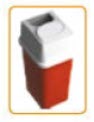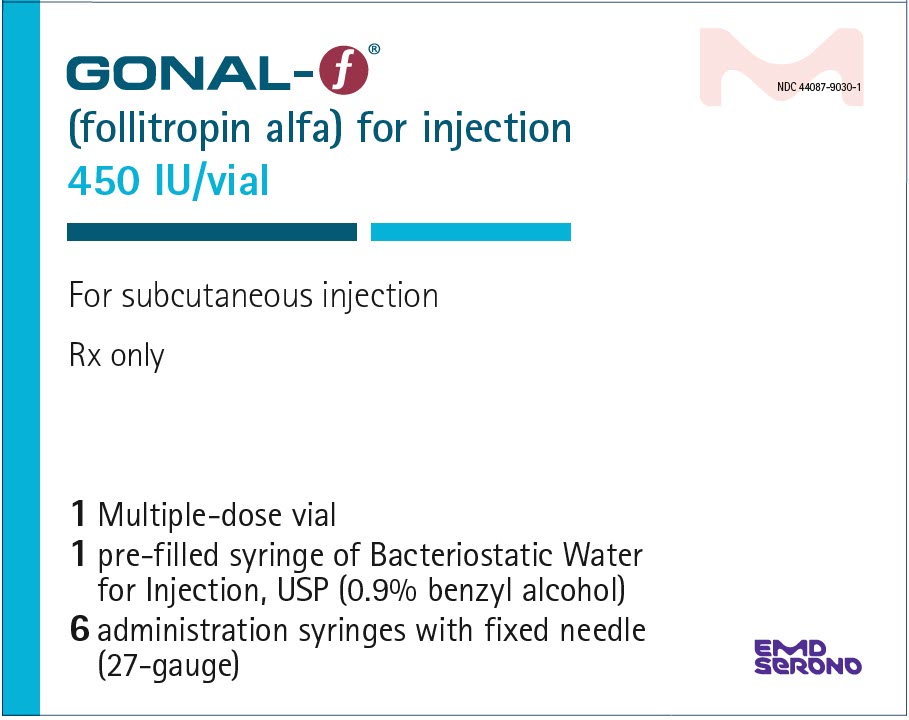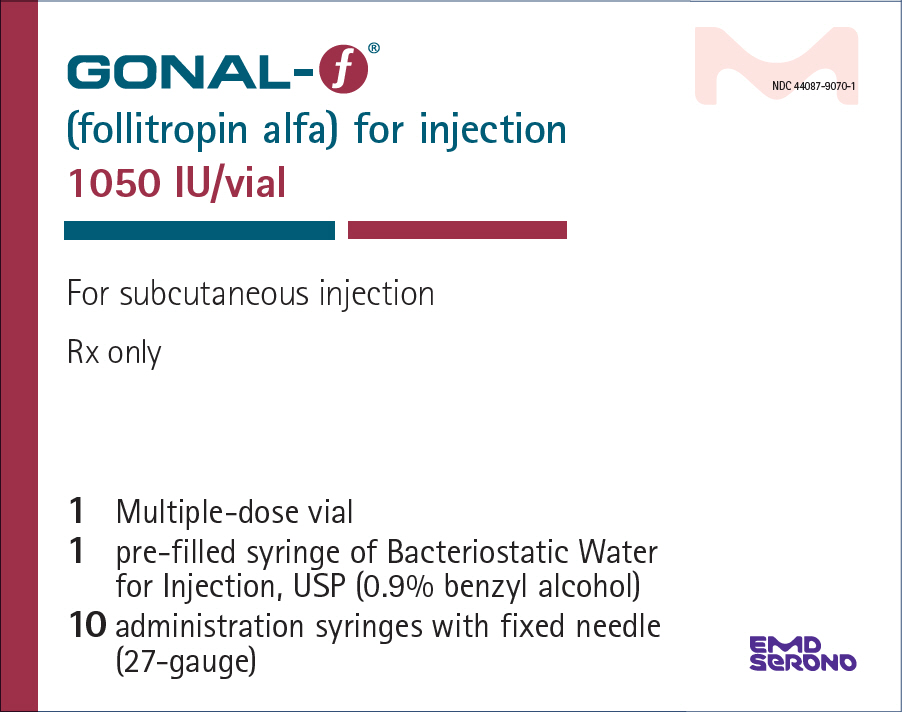 DRUG LABEL: Gonal-f
NDC: 44087-9030 | Form: KIT | Route: SUBCUTANEOUS
Manufacturer: EMD Serono, Inc.
Category: prescription | Type: HUMAN PRESCRIPTION DRUG LABEL
Date: 20250902

ACTIVE INGREDIENTS: FOLLITROPIN 450 [iU]/1 mL
INACTIVE INGREDIENTS: SUCROSE 30 mg/1 mL; SODIUM PHOSPHATE, DIBASIC, DIHYDRATE 1.11 mg/1 mL; SODIUM PHOSPHATE, MONOBASIC, MONOHYDRATE 0.45 mg/1 mL; PHOSPHORIC ACID; SODIUM HYDROXIDE; WATER 1 mL/1 mL; BENZYL ALCOHOL

HIGHLIGHTS OF PRESCRIBING INFORMATION

These highlights do not include all the information needed to use GONAL-f® safely and effectively. See full prescribing information for GONAL-f®
GONAL-f® (follitropin alfa) for injection, for subcutaneous use
Initial U.S. Approval: 1997

1 INDICATIONS AND USAGE

GONAL-f is a gonadotropin indicated for:

- Women:
  - Induction of ovulation and pregnancy in oligo-anovulatory infertile women for whom the cause of infertility is functional and not due to primary ovarian failure. (1.1)
  - Development of multiple follicles in ovulatory infertile women as part of Assisted Reproductive Technology (ART) cycles. (1.2)
- Men:
  - Induction of spermatogenesis in infertile men with primary and secondary hypogonadotropic hypogonadism for whom the cause of infertility is not due to primary testicular failure. (1.3)

2 DOSAGE AND ADMINISTRATION

Induction of Ovulation (2.3)

- Initial starting dose of the first cycle - 75 International Units of GONAL-f per day for 14 days, administered subcutaneously
- Individualize doses after 14 days
- Do not administer doses greater than 300 International Units per day

Development of Multiple Follicles in Assisted Reproductive Technology (ART) (2.3)

- Initial starting dose of the first cycle - 150 International Units per day, administered subcutaneously
- Dosage adjustments after 3 to 5 days and by 75 to 150 International Units at each adjustment
- Do not administer doses greater than 450 International Units per day

Males with Hypogonadotropic Hypogonadism and Azoospermia (2.4)

- Use in conjunction with hCG.
- Prior to concomitant therapy with GONAL-f and hCG, pretreat with 1,000 to 2,250 USP units of hCG alone two to three times per week to achieve normal serum testosterone levels, which may take 3 to 6 months.
- After normalization of serum testosterone, administer 150 International Units of GONAL-f subcutaneously three times a week and 1,000 USP units of hCG (or the dose required to maintain serum testosterone levels within the normal range) three times a week.

3 DOSAGE FORMS AND STRENGTHS

- For Injection: 450 International Units in a multiple-dose vial.(3)
- For Injection: 1050 International Units in a multiple-dose vial. (3)

4 CONTRAINDICATIONS

GONAL-f is contraindicated in women and men who exhibit (4):

- Prior hypersensitivity to recombinant FSH products or one of their excipients
- High levels of FSH indicating primary gonadal failure
- Uncontrolled non-gonadal endocrinopathies
- Sex hormone dependent tumors of the reproductive tract and accessory organs
- Tumors of pituitary gland or hypothalamus

GONAL-f is also contraindicated in women who exhibit (4):

- Abnormal uterine bleeding of undetermined origin
- Ovarian cyst or enlargement of undetermined origin

5 WARNINGS AND PRECAUTIONS

- Hypersensitivity Reactions and Anaphylaxis: If occurs, initiate appropriate therapy including supportive measures, and discontinue GONAL-f (5.1)
- Ovarian Hyperstimulation Syndrome: If serious, stop gonadotropins, including hCG, and determine if the woman needs to be hospitalized. Treatment is primarily symptomatic and consists of bed rest, fluid and electrolyte management, and analgesics (5.2)
- Pulmonary and Vascular Complications: In women with recognized risk factors, the benefits of induction of ovulation and ART need to be weighed against the risks. During or after use of GONAL-f, monitor for venous or arterial thromboembolic events (5.3)
- Ovarian Torsion: Early diagnosis and immediate detorsion limit damage to the ovary due to reduced blood supply (5.4)
- Abnormal Ovarian Enlargement: If the ovaries are abnormally enlarged on the last day of GONAL-f therapy, inform women not to administer hCG and to avoid intercourse (5.5)
- Multi-fetal Gestation and Births: The rate of multiple births is dependent on the number of embryos transferred. Advise the woman and her partner of the potential risk of multi-fetal gestation and birth before beginning therapy with GONAL-f (5.6)
- Embryofetal Toxicity: Inform women that the incidence of congenital malformations (birth defects) after some Assisted Reproductive Technology (ART) [specifically in vitro fertilization (IVF) or intracytoplasmic sperm injection (ICSI)] may be slightly higher than after spontaneous conception. There is no evidence that the use of gonadotropins during IVF or ICSI is associated with an increased risk of congenital malformations (5.7)
- Ectopic Pregnancy: Advise women who become pregnant following ART and have: abdominal/pelvic pain (particularly on one side); shoulder, neck or rectal pain; and nausea and vomiting to seek immediate medical attention. Confirm the presence of an intrauterine pregnancy early by β-hCG testing and transvaginal ultrasound (5.8)
- Spontaneous Abortion: The risk of spontaneous abortion (miscarriage) is increased with gonadotropin products, however, causality has not been established (5.9)
- Ovarian Neoplasm: Both benign and malignant ovarian neoplasms are reported in women who have had multiple drug therapy for controlled ovarian stimulation, however, causality has not been established (5.10)

6 ADVERSE REACTIONS

- The most common adverse reactions (≥5%) in ovulation induction include: ovarian cyst, headache, abdominal pain, OHSS, nausea, flatulence, pain and intermenstrual bleeding. (6.1)
- The most common adverse reactions (≥5%) in development of multiple follicles in ART include: headache, nausea, pelvic pain and abdominal pain. (6.1)
- The most common adverse reactions (>5%) in hypogonadotropic hypogonadal men participating in induction of spermatogenesis include: acne, injection site pain, fatigue, gynecomastia and seborrhea. (6.1)

To report SUSPECTED ADVERSE REACTIONS, contact EMD Serono at 1-800-283-8088, Ext 5563 or FDA at 1-800-FDA-1088 or www.fda.gov/medwatch.

8 USE IN SPECIFIC POPULATIONS

- Lactation: Advise not to breastfeed (8.2)

FULL PRESCRIBING INFORMATION

1 INDICATIONS AND USAGE

GONAL-f is indicated for:

2 DOSAGE AND ADMINISTRATION

2.1 Important Dosage and Administration Information

Only physicians who are experienced in infertility treatment, should treat women with GONAL-f. GONAL-f is a gonadotropin product capable of causing in women, Ovarian Hyperstimulation Syndrome (OHSS) with or without pulmonary or vascular complications [see Warnings and Precautions (5.2, 5.3)] and multiple births [see Warnings and Precautions (5.6)]. Gonadotropin therapy requires the availability of appropriate monitoring facilities [see Warnings and Precautions (5.11)]. Use the lowest effective dose of GONAL-f.

Give careful attention to the diagnosis of infertility and the selection of candidates for GONAL-f therapy [see Dosage and Administration (2.3, 2.4)].

2.2 Preparation of GONAL-f and Selection of Injection Site

- Store lyophilized multiple-dose vials refrigerated or at room temperature (2°-25°C /36°-77°F) and protected from light.
- Prior to administration, parenteral drug products should be inspected visually for particulate matter and discoloration, whenever solution and container permit.
- Instruct women and men to use the accompanying syringes, calibrated in International Units FSH for administration. The 27-gauge injection syringe (see figure below) has unit dose markings from 37.5 International Units to 600 International Units FSH for use with GONAL-f Multi-Dose. Instruct women and men to take a specific dose of GONAL-f Multi-Dose. Show women and men how to locate the syringe marking that corresponds to the prescribed dose.
- Each GONAL‑f Multi‑Dose Vial delivers 450 International Units or 1050 International Units of follitropin alfa, respectively
  - Multi-Dose 450 International Units Vial:
    - Dissolve the contents of one Multi-Dose vial (450 International Units) with 1 mL Bacteriostatic Water for Injection (0.9% benzyl alcohol), USP. Resulting concentration will be 600 International Units/mL. Following reconstitution as directed, product will deliver the equivalent of six 75 International Units doses.
  - Multi-Dose 1050 International Units Vial:
    - Dissolve the contents of one Multi-Dose vial (1050 International Units) with 2 mL Bacteriostatic Water for Injection (0.9% benzyl alcohol), USP. Resulting concentration will be 600 International Units/mL. Following reconstitution as directed, product will deliver the equivalent of fourteen 75 International Units doses.
- Discard unused reconstituted solution after 28 days.
- Administer GONAL-f subcutaneously in the abdomen, upper arm, or upper leg as described in Patient Information and Instructions for Use.

2.3 Dosing for Ovulation Induction

Prior to initiation of treatment with GONAL-f:

- Perform a complete gynecologic and endocrinologic evaluation
- Exclude primary ovarian failure
- Exclude the possibility of pregnancy
- Demonstrate tubal patency
- Evaluate the fertility status of the male partner

The dosing scheme is stepwise and is individualized for each woman [see Clinical Studies (14.1)].

- Administer a starting dose of 75 International Units of GONAL-f subcutaneously daily for 14 days in the first cycle of use.
- In subsequent cycles of treatment, determine the starting dose (and dosage adjustments) of GONAL-f based on the woman's history of the ovarian response to GONAL-f.
- If indicated by the ovarian response after the initial 14 days, make an incremental adjustment in dose of up to 37.5 International Units.
- If indicated by the ovarian response, make additional incremental adjustments in the dose, up to 37.5 International Units, every 7 days.
- Continue treatment until follicular growth and/or serum estradiol levels indicate an adequate ovarian response.
- Consider the following when planning the woman's individualized dose:
  - Use the lowest dose of GONAL-f consistent with the expectation of good results.
  - Use appropriate GONAL-f dose adjustment(s) to prevent multiple follicular growth and cycle cancellation.
  - The maximum, individualized, daily dose of GONAL-f is 300 International Units per day.
  - In general, do not exceed 35 days of treatment, unless an estradiol rise indicates imminent follicular development.
- When pre-ovulatory conditions are reached, administer human chorionic gonadotropin (hCG) to induce final oocyte maturation and ovulation. Human chorionic gonadotropin, hCG, (5,000 USP units) should be given 1 day after the last dose of GONAL-f.
- Encourage the woman and her partner to have intercourse daily, beginning on the day prior to the administration of hCG and until ovulation becomes apparent.
- Withhold hCG in cases where the ovarian monitoring suggests an increased risk of ovarian hyperstimulation syndrome (OHSS) on the last day of GONAL-f therapy (for example estradiol greater than 2,000 pg per mL) [see Warnings and Precautions (5.2, 5.3, 5.5, 5.11)].
  - Discourage intercourse when the risk for OHSS is increased [see Warnings and Precautions (5.2, 5.5)].
- Schedule a follow-up visit in the luteal phase.
- Individualize the initial dose administered in subsequent cycles based on the woman's response in the preceding cycle.
- As in the initial cycle, do not administer doses larger than 300 International Units of FSH per day. Administer 5,000 USP units of hCG 1 day after the last dose of GONAL-f to complete follicular development and induce ovulation.
- Follow the above recommendations to minimize the chance of development of OHSS.

2.4 Dosing for Multiple Follicle Development as part of an Assisted Reproductive Technology (ART) Cycle

Prior to initiation of treatment with GONAL-f:

- Perform a complete gynecologic and endocrinologic evaluation, and diagnose the cause of infertility
- Exclude the possibility of pregnancy
- Evaluate the fertility status of the male partner

The dosing scheme follows a stepwise approach and is individualized for each woman.

- Beginning on cycle day 2 or 3, administer subcutaneously a starting dose of 150 International Units of GONAL-f daily until sufficient follicular development, as determined by ultrasound in combination with measurement of serum estradiol levels, is attained. In most cases, therapy should not exceed ten days.
- In women whose endogenous gonadotropin levels are suppressed, initiate GONAL-f administration at a dose of 225 International Units per day.
- Adjust the dose after 5 days based on the woman's ovarian response, as determined by ultrasound evaluation of follicular growth and serum estradiol levels.
- Do not make additional dosage adjustments more frequently than every 3-5 days or by more than 75-150 International Units at each adjustment.
- Continue treatment until adequate follicular development is evident, and then administer hCG (5,000 to 10,000 USP units) to induce final follicular maturation in preparation for oocyte retrieval.
- Withhold hCG administration in cases where the ovarian monitoring suggests an increased risk of OHSS on the last day of GONAL-f therapy [see Warnings and Precautions (5.2, 5.3, 5.4, 5.11)].
- Do not use doses greater than 450 International Units per day.

2.5 Dosing for Induction of Spermatogenesis in Males with Azoospermia and Primary or Secondary Hypogonadotropic Hypogonadism:

Prior to initiation of treatment with GONAL-f:

- Confirm azoospermia
- Perform a thorough medical and endocrinologic evaluation to exclude other treatable etiologies of azoospermia
- Confirm hypogonadotropic hypogonadism
- Exclude primary testicular failure
- Normalize serum testosterone levels

The dosing scheme follows a stepwise approach and is individualized for each man.

- GONAL-f must be given in conjunction with hCG.
- Prior to concomitant therapy with GONAL-f and hCG, pretreatment with hCG alone (1,000 to 2,250 USP units two to three times per week) is required to normalize serum testosterone levels.
- Treatment with hCG alone should continue until serum testosterone levels reach the normal range, which may take 3 to 6 months. The dose of hCG may also need to be increased during this time to achieve normal serum testosterone levels.
- After serum testosterone levels have normalized, administer GONAL-f 150 International Units subcutaneously three times a week and hCG 1,000 USP units (or the dose required to maintain serum testosterone levels within the normal range) three times a week. The lowest dose of GONAL-f which induces spermatogenesis should be utilized.
- If azoospermia persists, increase the dose of GONAL-f up to a maximum dose of 300 International Units three times per week. Administer GONAL-f for up to 18 months to achieve adequate spermatogenesis.

2.6 Missed Dose

Do not double the next dose if a woman or a man misses or forgets to take a dose of GONAL-f.

3 DOSAGE FORMS AND STRENGTHS

- For Injection: 450 International Units of white lyophilized powder in a multiple-dose vial
- For Injection: 1050 International Units of white lyophilized powder in a multiple-dose vial

4 CONTRAINDICATIONS

GONAL-f is contraindicated in women and men who exhibit:

- Prior hypersensitivity to recombinant FSH products or one of their excipients. Reactions have included anaphylaxis [see Warning and Precautions (5.1)]
- High levels of FSH indicating primary gonadal failure
- The presence of uncontrolled non-gonadal endocrinopathies (for example, thyroid, adrenal, or pituitary disorders)
- Sex hormone dependent tumors of the reproductive tract and accessory organs
- Tumors of pituitary gland or hypothalamus

GONAL-f is also contraindicated in women who exhibit:

- Abnormal uterine bleeding of undetermined origin
- Ovarian cyst or enlargement of undetermined origin

5 WARNINGS AND PRECAUTIONS

5.1 Hypersensitivity Reactions and Anaphylaxis

In the post-marketing experience, serious systemic hypersensitivity reactions, including anaphylaxis, have been reported with use of GONAL-f and GONAL-f RFF. Symptoms have included dyspnea, facial edema, pruritus, and urticaria. If an anaphylactic or other serious allergic reaction occurs, initiate appropriate therapy including supportive measures if cardiovascular instability and/or respiratory compromise occur, and discontinue further use.

5.2 Ovarian Hyperstimulation Syndrome (OHSS)

Ovarian Hyperstimulation Syndrome (OHSS) is a medical entity distinct from uncomplicated ovarian enlargement and may progress rapidly to become a serious medical event. OHSS is characterized by a dramatic increase in vascular permeability, which can result in a rapid accumulation of fluid in the peritoneal cavity, thorax, and potentially, the pericardium. The early warning signs of development of OHSS are severe pelvic pain, nausea, vomiting, and weight gain. Abdominal pain, abdominal distension, gastrointestinal symptoms including nausea, vomiting and diarrhea, severe ovarian enlargement [see Warnings and Precautions (5.6)], weight gain, dyspnea, and oliguria have been reported with OHSS. Clinical evaluation may reveal hypovolemia, hemoconcentration, electrolyte imbalances, ascites, hemoperitoneum, pleural effusions, hydrothorax, acute pulmonary distress, and thromboembolic reactions [see Warnings and Precautions (5.4)]. Transient liver function test abnormalities suggestive of hepatic dysfunction with or without morphologic changes on liver biopsy, have been reported in association with OHSS.

OHSS occurs after gonadotropin treatment has been discontinued and it can develop rapidly, reaching its maximum about seven to ten days following treatment. Usually, OHSS resolves spontaneously with the onset of menses. If there is evidence that OHSS may be developing prior to hCG administration [see Dosage and Administration (2.2, 2.3)], withhold hCG. Cases of OHSS are more common, more severe, and more protracted if pregnancy occurs; therefore, assess women for the development of OHSS for at least two weeks after hCG administration.

If serious OHSS occurs, stop gonadotropins, including GONAL-f and hCG, and consider whether the woman needs to be hospitalized. Treatment is primarily symptomatic and overall consists of bed rest, fluid and electrolyte management, and analgesics (if needed). Because the use of diuretics can accentuate the diminished intravascular volume, avoid diuretics except in the late phase of resolution as described below. The management of OHSS is divided into three phases as follows:

- Acute Phase:
  Management is directed at preventing hemoconcentration due to loss of intravascular volume to the third space and minimizing the risk of thromboembolic phenomena and kidney damage. Thoroughly assess daily or more often, based on the clinical need, fluid intake and output, weight, hematocrit, serum and urinary electrolytes, urine specific gravity, BUN and creatinine, total proteins with albumin: globulin ratio, coagulation studies, electrocardiogram to monitor for hyperkalemia, and abdominal girth. Treatment, consisting of limited intravenous fluids, electrolytes, human serum albumin, is intended to normalize electrolytes while maintaining an acceptable but somewhat reduced intravascular volume. Full correction of the intravascular volume deficit may lead to an unacceptable increase in the amount of third space fluid accumulation.
- Chronic Phase:
  After the acute phase is successfully managed as above, excessive fluid accumulation in the third space should be limited by instituting severe potassium, sodium, and fluid restriction.
- Resolution Phase:
  As third space fluid returns to the intravascular compartment, a fall in hematocrit and increasing urinary output are observed in the absence of any increase in intake. Peripheral and/or pulmonary edema may result if the kidneys are unable to excrete third space fluid as rapidly as it is mobilized. Diuretics may be indicated during the resolution phase, if necessary, to combat pulmonary edema.
  Do not remove ascitic, pleural, and pericardial fluid, unless there is the necessity to relieve symptoms such as pulmonary distress or cardiac tamponade.

OHSS increases the risk of injury to the ovary. Avoid pelvic examination or intercourse, as these may cause rupture of an ovarian cyst, which may result in hemoperitoneum.

If bleeding occurs and requires surgical intervention, control the bleeding and retain as much ovarian tissue as possible. A physician experienced in the management of this syndrome, or who is experienced in the management of fluid and electrolyte imbalances should be consulted.

5.3 Pulmonary and Vascular Complications

Serious pulmonary conditions (for example, atelectasis, acute respiratory distress syndrome and exacerbation of asthma) have been reported in women treated with gonadotropins, including GONAL-f. In addition, thromboembolic events both in association with, and separate from OHSS have been reported in women treated with gonadotropins, including GONAL-f. Intravascular thrombosis and embolism, which may originate in venous or arterial vessels, can result in reduced blood flow to critical organs or the extremities. Women with generally recognized risk factors for thrombosis, such as personal or family history, severe obesity, or thrombophilia, may have an increased risk of venous or arterial thromboembolic events, during or following treatment with gonadotropins. Sequelae of such reactions have included venous thrombophlebitis, pulmonary embolism, pulmonary infarction, cerebral vascular occlusion (stroke), and arterial occlusion resulting in loss of limb and rarely in myocardial infarctions. In rare cases, pulmonary complications and/or thromboembolic reactions have resulted in death. In women with recognized risk factors, the benefits of ovulation induction and Assisted Reproductive Technology (ART) need to be weighed against the risks. It should be noted that pregnancy also carries an increased risk of thrombosis.

5.4 Ovarian Torsion

Ovarian torsion has been reported after treatment with gonadotropins, including GONAL-f. This may be related to OHSS, pregnancy, previous abdominal surgery, past history of ovarian torsion, previous or current ovarian cyst and polycystic ovaries. Early diagnosis and immediate detorsion limit damage to the ovary due to reduced blood supply.

5.5 Abnormal Ovarian Enlargement

In order to minimize the hazards associated with abnormal ovarian enlargement that may occur with GONAL-f therapy, individualize treatment and use the lowest effective dose [see Dosage and Administration (2.2, 2.3)]. Use of ultrasound monitoring of ovarian response and/or measurement of serum estradiol levels is important to minimize the risk of ovarian stimulation [see Warnings and Precautions (5.12)].

If the ovaries are abnormally enlarged on the last day of GONAL-f therapy, do not administer hCG in order to reduce the chance of developing Ovarian Hyperstimulation Syndrome (OHSS) [see Warnings and Precautions (5.2)]. Prohibit intercourse for women with significant ovarian enlargement after ovulation because of the danger of hemoperitoneum resulting from rupture of ovarian cysts [see Warnings and Precautions (5.2)].

5.6 Multi-fetal Gestation and Birth

Multi-fetal gestation and births have been reported with all gonadotropin therapy, including therapy with GONAL-f.

During clinical trials with GONAL-f, multiple births occurred in 20% of live births in women receiving therapy for ovulation induction and 35.1% of live births in women undergoing ART. Advise the woman and her partner of the potential risk of multi-fetal gestation and birth before beginning therapy with GONAL-f.

5.7 Embryofetal toxicity

The incidence of congenital malformations after some ART [specifically in vitro fertilization (IVF) or intracytoplasmic sperm injection (ICSI)] may be slightly higher than after spontaneous conception. This slightly higher incidence is thought to be related to differences in parental characteristics (e.g., maternal age, maternal and paternal genetic background, sperm characteristics) and to the higher incidence of multi-fetal gestations after IVF or ICSI. There are no indications that the use of gonadotropins during IVF or ICSI is associated with an increased risk of congenital malformations.

5.8 Ectopic Pregnancy

Since infertile women undergoing ART often have tubal abnormalities, the incidence of ectopic pregnancy may be increased in women who become pregnant as a result of ART. Advise women who become pregnant following ART and have: abdominal/pelvic pain (particularly on one side); shoulder, neck or rectal pain; and nausea and vomiting to seek immediate medical attention. Confirm the presence of an intrauterine pregnancy early by β-hCG testing and transvaginal ultrasound.

5.9 Spontaneous Abortion

The risk of spontaneous abortion (miscarriage) is increased with gonadotropin products, including GONAL-f. However, causality has not been established. The increased risk may be a factor of the underlying infertility.

5.10 Ovarian Neoplasms

There have been infrequent reports of ovarian neoplasms, both benign and malignant, in women who have had multiple drug therapy for controlled ovarian stimulation, however, a causal relationship has not been established.

5.11 Laboratory Tests

In most instances, treatment of women with GONAL-f will result only in follicular recruitment and development. In the absence of an endogenous LH surge, hCG is given to trigger ovulation when monitoring of the woman indicates that sufficient follicular development has occurred. This may be estimated by ultrasound alone or in combination with measurement of serum estradiol levels. The combination of both ultrasound and serum estradiol measurement are useful for monitoring follicular growth and maturation, timing of the ovulatory trigger, detecting ovarian enlargement and minimizing the risk of the OHSS and multiple gestation.

The clinical confirmation of ovulation is obtained by direct or indirect indices of progesterone production as well as sonographic evidence of ovulation.

Direct or indirect indices of progesterone production:

- Urinary or serum luteinizing hormone (LH) rise
- A rise in basal body temperature
- Increase in serum progesterone
- Menstruation following a shift in basal body temperature

Sonographic evidence of ovulation:

- Collapsed follicle
- Fluid in the cul-de-sac
- Features consistent with corpus luteum formation
- Secretory endometrium

6 ADVERSE REACTIONS

The following serious adverse reactions are discussed elsewhere in the labeling:

- Hypersensitivity Reactions and Anaphylaxis [see Warnings and Precautions (5.1)]
- Ovarian Hyperstimulation Syndrome [see Warnings and Precautions (5.2)]
- Pulmonary and Vascular Complication [see Warnings and Precautions (5.3)]
- Ovarian Torsion [see Warnings and Precautions (5.4)]
- Abnormal Ovarian Enlargement [see Warnings and Precautions (5.5)]
- Multi-fetal Gestation and Birth [see Warnings and Precautions (5.6)]
- Embryofetal Toxicity [see Warnings and Precautions (5.7)]
- Ectopic Pregnancy [see Warnings and Precautions (5.8)]
- Spontaneous Abortion [see Warnings and Precautions (5.9)]
- Ovarian Neoplasms [see Warnings and Precautions (5.10)]

6.1 Clinical Study Experience

Because clinical trials are conducted under widely varying conditions, adverse reaction rates observed in the clinical trials of a drug cannot be directly compared to rates in the clinical trial of another drug and may not reflect the rates observed in practice.

Women:

The safety of GONAL-f was examined in four clinical trials that enrolled 691 women [two trials for ovulation induction (454 women) and two trials for ART (237 women)].

Induction of Ovulation

In a randomized, open-labeled, multicenter, active-controlled trial in oligo-anovulatory infertile women, conducted in the U.S., a total of 118 oligo-anovulatory infertile women were randomized to and underwent ovulation induction with GONAL-f versus a comparator urofollitropin. Adverse reactions occurring in at least 5.0% of women receiving GONAL-f are listed in Table 1.

Table 1: Common Adverse Reactions Reported at a Frequency of ≥ 5% in an U.S. Ovulation Induction Trial
System Organ Class/Adverse Reactions | GONAL-f N=118 [total number of women treated with GONAL-f] (288 treatment cycles [up to 3 treatment cycles per woman]) n [number of women with the adverse reaction] (%)
Body as a Whole - General
Pain | 6 (5.1%)
Central and Peripheral Nervous System
Headache | 12 (10.2%)
Gastrointestinal System
Abdominal Pain | 9 (7.6%)
Nausea | 7 (5.9%)
Flatulence | 7 (5.9%)
Reproductive, Female
Intermenstrual Bleeding | 6 (5.1)
Ovarian Hyperstimulation | 8 (6.8%)
Ovarian Cyst | 17 (14.4%)

Development of Multiple Follicles as part of an Assisted Reproductive Technology (ART) Cycle

In a randomized, open-labeled, active-comparator trial conducted in the U.S., a total of 56 normal ovulatory infertile women were randomized and received GONAL-f versus a urofollitropin comparator as part of an ART [in vitro fertilization (IVF) or intracytoplasmic sperm injection cycle (ICSI)] cycle. All women received pituitary down-regulation with gonadotropin releasing hormone (GnRH) agonist before stimulation. Adverse Reactions occurring in at least 5.0% of women are listed in Table 2.

Table 2: Common Adverse Reactions Reported at a Frequency of ≥ 5% in an U.S. ART Trial
System Organ Class/Adverse Reactions | GONAL-f (N=56 [total number of women treated with GONAL-f]) n [number of women with the adverse reaction] (%)
Central and Peripheral Nervous System
Headache | 7 (12.5%)
Gastrointestinal System
Abdominal Pain | 3 (5.4%)
Nausea | 4 (7.1%)
Reproductive, Female
Pelvic Pain | 4 (7.1)

Induction of Spermatogenesis:

The safety of GONAL-f for induction of spermatogenesis in men with primary or secondary hypogonadotropic hypogonadism was examined in 3 open-label, non-randomized, multi-center, multi-national, escalating dose clinical trials (Trials 1, 2 and 3) conducted in 76 adult men (aged 16 to 48 years) with primary or secondary hypogonadotropic hypogonadism (defined as serum testosterone <100 ng/mL and low or normal FSH and LH) and azoospermia (sperm concentration <0.1×10^6/mL). Of the 76 men enrolled, 63 received treatment with GONAL-f.

During these trials, there was one serious adverse reaction of gynecomastia requiring surgical excision of breast tissue in a 50 year old man who received 9 months of therapy with GONAL-f. Pathology report showed gynecomastia with no atypia.

There were no discontinuations due to adverse reactions.

Adverse reactions reported in Trials 1, 2 and 3 by ≥2 patients during treatment with GONAL-f are shown in Table 3.

Table 3. Common Adverse Reactions in Men with Azoospermia and Primary or Secondary Hypogonadotropic Hypogonadism Receiving GONAL-f in Trials 1, 2 and 3 for Induction for Spermatogenesis
 | N=63 n (%)
Acne | 17 (27)
Injection site pain | 7 (11)
Gynecomastia | 4 (6)
Seborrhea | 3 (5)
Fatigue | 6 (10)
Libido decreased | 2 (3)

6.2 Postmarketing Experience

In addition to adverse events reported from clinical trials, the following adverse reactions have been reported during postmarketing use of GONAL-f. Because these reactions were reported voluntarily from a population of uncertain size, the frequency or a causal relationship to GONAL-f cannot be reliably determined.

Body as a Whole - General: Hypersensitivity reactions including anaphylaxis

Respiratory System: Asthma exacerbation

Vascular Disorders: Thromboembolism

8 USE IN SPECIFIC POPULATIONS

8.1 Pregnancy

Risk Summary

GONAL-f is not indicated in pregnant women.

The incidence of congenital malformations after some Assisted Reproductive Technology, specifically in vitro fertilization (IVF) or intracytoplasmic sperm injection (ICSI), may be slightly higher than that after spontaneous conception. This slightly higher incidence is thought to be related to differences in parental characteristics (e.g., maternal age, maternal and paternal genetic background, sperm characteristics) and to a higher incidence of multi-fetal gestations after IVF or ICSI. There is no human data that the use of gonadotropins (including GONAL-f) alone or as part of IVF or ICSI cycles, increases the risk of congenital malformations.

The risk of spontaneous abortion (miscarriage) is increased in women who have used gonadotropin products (including GONAL-f) to achieve pregnancy.

In animal studies, the continuous administration of recombinant human FSH during pregnancy resulted in a decrease in the number of viable fetuses and difficult and prolonged delivery. No teratogenic effect has been observed.

In the U.S. general population, the estimated background risk of major birth defects and miscarriage in clinically recognized pregnancies is 2 to 4% and 15 to 20%, respectively.

Data

Human Data

Data on a limited number of exposed pregnancies indicate no adverse reactions of gonadotropins on pregnancy, embryonal or fetal development, parturition or postnatal development following controlled ovarian stimulation.

Animal Data

Embryofetal development studies with recombinant human FSH in rats, where dosing occurred during organogenesis, showed a dose dependent increase in difficult and prolonged parturition in dams, and dose dependent increases in resorptions, pre- and post-implantation losses, and stillborn pups at doses representing 5 and 41 times the lowest clinical dose of 75 International Units based on body surface area. Pre-/post-natal development studies with recombinant human FSH in rats, where dosing occurred from mid-gestation through lactation, showed difficult and prolonged parturition in all dams dosed at 41 times the lowest clinical dose of 75 International Units based on body surface area, along with maternal death and stillborn pups associated with the difficult and prolonged parturition. This toxicity was not observed in dams and offspring dosed at a level 5 times the lowest clinical dose of 75 International Units based on body surface area.

8.2 Lactation

There are no data on the presence of GONAL-f in human milk, the effects on the breastfed infant, or the effects on milk production. Because the secretion of prolactin during lactation can result in inadequate response to ovarian stimulation, advise women not to breast feed during treatment with GONAL-f.

8.3 Females and Males of Reproductive Potential

Because GONAL-f is not indicated in pregnant women, verify a negative pregnancy test before administering GONAL-f to a woman [see Dosage and Administration (2.3, 2.4)].

8.4 Pediatric Use

Safety and effectiveness in pediatric patients have not been established.

8.5 Geriatric Use

Safety and effectiveness of GONAL-f in postmenopausal women have not been established and it is not indicated in this population.

10 OVERDOSAGE

Ovarian hyperstimulation syndrome (OHSS) and multiple gestations have been observed in women with GONAL-f overdosage [see Warnings and Precautions (5.2, 5.6)].

11 DESCRIPTION

Follitropin alfa, a gonadotropin [human follicle stimulating hormone (hFSH)], is a glycoprotein hormone produced by recombinant DNA technology in a Chinese Hamster Ovary (CHO) cell line. It has a dimeric structure containing two glycoprotein subunits (alpha and beta). The alpha and beta subunits have 92 and 111 amino acids, respectively, and their primary and tertiary structures are indistinguishable from those of human follicle stimulating hormone. The molecular weight is approximately 31 kDa (14 kDa for alpha subunit and 17 kDa for beta subunit).

GONAL-f (follitropin alfa) for injection is a sterile, lyophilized powder intended for subcutaneous injection after reconstitution.

Each multiple-dose vial of GONAL-f containing either 450 International Units (33 mcg) or 1050 International Units (77 mcg) follitropin alfa and the inactive ingredients dibasic sodium phosphate (0.89 mg), monobasic sodium phosphate (0.39 mg), and sucrose (30 mg). Phosphoric acid and/or sodium hydroxide may be used prior to lyophilization for pH adjustment. After reconstitution with supplied 1 mL of with Bacteriostatic Water for Injection (0.9% benzyl alcohol), USP, the resultant concentration is 600 IU/mL with a pH of approximately 6.5 to 7.5.

Under current storage conditions, GONAL-f may contain up to 10% of oxidized follitropin alfa.

12 CLINICAL PHARMACOLOGY

12.1 Mechanism of Action

GONAL-f stimulates ovarian follicular growth in women who do not have primary ovarian failure. In order to bring about final maturation of the follicle and ovulation in the absence of an endogenous LH surge, human chorionic gonadotropin (hCG) must be given, following the administration of GONAL-f, when monitoring of the patient indicates that sufficient follicular development is achieved.

GONAL-f stimulates spermatogenesis in men with hypogonadotropic hypogonadism when administered with hCG.

12.2 Pharmacodynamics

Serum inhibin, estradiol, and total follicular volume responded as a function of time, with pronounced inter-woman variability in healthy volunteers administered GONAL-f. Pharmacodynamic effect lagged behind FSH serum concentration. Serum inhibin levels responded with the least delay and declined rapidly after discontinuation of GONAL-f. Follicular growth was most delayed and continued even after discontinuation of GONAL-f, and after serum FSH levels had declined. Maximum follicular volume correlated better with inhibin and estradiol peak levels than with FSH concentration. Inhibin rise was an early index of follicular development.

FSH serum levels following fixed (during the first five days) and then adjusted doses of GONAL-f were found to be poor predictors of follicular growth rate. High pre-treatment serum FSH levels may predict lower follicular growth rates.

Inhibin levels reached a plateau during the entire administration period and then returned to baseline despite high inter-male variation and the absence of down-regulation in healthy male volunteers administered GONAL-f.

12.3 Pharmacokinetics

Single dose and state-state pharmacokinetics of follitropin alfa were determined following subcutaneous administration of GONAL-f to healthy, down-regulated female volunteers, healthy adult male volunteers, and pituitary down-regulated women undergoing in vitro fertilization and embryo transfer (IVF/ET). The pharmacokinetic parameters of follitropin alfa following subcutaneous administration of GONAL-f are presented in Table 4.

Table 4: Pharmacokinetic Parameters (mean ± SD) of Follitropin Alfa
Population | Female |  |  | Male
Population | Healthy Female Volunteers |  | IVF/ET Patients | Healthy Male Volunteers
Dose (IU) | Single Dose (150 IU) | Multiple Dose (7 × 150 IU) | Multiple Dose (5 × 225 IU), | Single Dose (225 IU) | Multiple Dose (7 × 225 IU)
General Information
AUC (IU*hr/L) | 176 ± 87 | 187 ± 61 [Steady-state AUC144 hr-168 hr (after the 7th daily subcutaneous dose)] | --- | 220 ± 109 | 186 ± 23
Cmax (IU/L) | 3 ± 1 | 9 ± 3 | --- | 2.5 ± 0.8 | 8.3 ± 0.9
Absorption
Absolute Bioavailability (%) | 66 ± 39 | --- |  | --- | ---
Tmax (hr) | 16 ± 10 | 8 ± 6 | --- | 20 ± 14 | 10.7 ± 6.7
Distribution
Apparent Vd (L) | ------ | --- | 10 ± 3 | --- | ---
Elimination [Follitropin alfa metabolism has not been studied in humans.]
t1/2 terminal (hr) [The elimination rate of follitropin alfa following subcutaneous administration is dependent on the absorption rate.] | 24 ± 11 | 24 ± 8 | 32 | 41 ± 14 | 32 ± 4
CL/F (L/hr) [The apparent clearance was comparable to that in healthy volunteers.] | ------ | --- | 0.7 ± 0.2 | 0.86 ± 0.48 | 0.90 ± 0.12
AUC=area under the concentration-time curve; CL/F=apparent clearance; Cmax=peak serum concentration; Tmax=time of Cmax; t1/2=half-life; Vd=volume of distribution

Specific Populations

Body Weight

The absorption rate of follitropin alfa lowers as body mass index (BMI) increases.

Drug Interaction Studies

No studies evaluating the drug interaction potential of follitropin alfa has been conducted.

13 NONCLINICAL TOXICOLOGY

13.1 Carcinogenesis, Mutagenesis, Impairment of Fertility

Long- term studies in animals have not been performed to evaluate the carcinogenic potential of GONAL-f. However, follitropin alfa showed no mutagenic activity in a series of tests performed to evaluate its potential genetic toxicity including, bacterial and mammalian cell mutation tests, a chromosomal aberration test and a micronucleus test.

Impaired fertility has been reported in rats, exposed to pharmacological doses of follitropin alfa (greater than or equal to 40 International Units per kg per day, greater than or equal to 5 times the lowest clinical dose of 75 International Units) for extended periods, through reduced fecundity.

14 CLINICAL STUDIES

14.1 Induction of Ovulation

The safety and efficacy of GONAL-f were examined in a randomized, open-label, multicenter, active-controlled trial conducted in the U.S. in oligo-anovulatory infertile women. Women were randomized to GONAL-f , administered subcutaneously, or a comparator urofollitropin product, administered intramuscularly.

The primary efficacy parameter was the ovulation rate. Two hundred and thirty-two women received treatment for up to three cycles with GONAL-f (118 women) or urofollitropin (114 women).

Ovulation results for women who received treatment with GONAL-f in at least one cycle are summarized in Table 5.

Table 5: Cumulative Ovulation and Clinical Pregnancy Rates in Induction of Ovulation Trial
Cycle | GONAL-f (n=118)
Cycle | Cumulative [Cumulative rates were determined per woman over cycles 1, 2, and 3.] Percent Ovulation | Cumulative Clinical Pregnancy [Clinical pregnancy was defined as a pregnancy for which a fetal sac (with or without heart activity) was visualized by ultrasound on day 34-36 after hCG administration.] Rate
Cycle 1 | 58% [Non-inferior to comparator recombinant human FSH based on a two-sided 95% confidence interval, intent-to-treat analysis.] | 13% [Secondary efficacy outcomes. The trial was not powered to demonstrate differences in these outcomes.]
Cycle 2 | 72% | 25%
Cycle 3 | 81% | 37

For the 44 woman in the GONAL-f group who achieved clinical pregnancy, 22.7% did not reach a term pregnancy, 63.6% had singleton births and 13.7% had multiple births.

An additional randomized, open-label, multinational, multicenter trial, active-comparator trial was conducted in oligo-anovulatory infertile women who failed to ovulate or conceive following adequate clomiphene citrate therapy. Results for the primary efficacy outcome of cumulative percent ovulation at Cycle 1 were similar to those presented in Table 5 for the U.S. ovulation induction trial.

14.2 Development of Multiple Follicles as part of an Assisted Reproductive Technology (ART) Cycle:

The efficacy of GONAL-f in ART, was evaluated in a randomized, open-label, multicenter, active-controlled trial conducted in the U.S., in ovulatory, infertile women undergoing stimulation of multiple follicles for In Vitro Fertilization (IVF) and Embryo Transfer (ET). All women received a gonadotropin releasing hormone (GnRH) agonist for pituitary down-regulation before randomization and administration of GONAL-f (n=56) or a comparator urofollitropin product (n=58). The primary efficacy endpoint was the number of mature pre-ovulatory follicles on the day of hCG administration. The trial was not powered to demonstrate differences in secondary outcomes.

Treatment outcomes for a single IVF cycle with controlled stimulation with GONAL-f are summarized in Table 6.

Table 6: Treatment Outcomes with GONAL-f in an In Vitro Fertilization Trial in Ovulatory Women
 | GONAL--f (n=56)
Mean number of follicles ≥ 14mm diameter on day of hCG [Primary efficacy outcome] (n=50) | 7.2
Mean number of oocytes recovered per patient [Secondary efficacy outcomes. The trial was not powered to demonstrate differences in these outcomes.] (n=49) | 9.3
Mean Serum E2 (pg/mL) on day of hCG (n=46) | 1221
Mean treatment duration in days (range) (n=56) | 10.1 (5-15)
Clinical pregnancy [Clinical pregnancy was defined as a pregnancy for which a fetal sac (with or without heart activity) was visualized by ultrasound on day 34-36 after hCG administration.] rate per attempt (n=56) | 20%
Clinical pregnancy rate per embryo transfer (n=47) | 23%

For the 11 women in the GONAL-f group who achieved clinical pregnancy, 36.3% did not reach a term pregnancy, 36.3% had singleton births and 27.3% had multiple births.

An additional randomized, open-label, multinational, multicenter study in ovulatory infertile women was conducted in non-U.S. countries. Women were randomized to receive either GONAL-f by subcutaneous administration (60 women) or urofollitropin by intramuscular administration (63 women) after down-regulation of the pituitary with a GnRH agonist. The primary efficacy parameter was the number of mature pre-ovulatory follicles on the day of hCG administration. Results over a single IVF cycle for the primary efficacy outcome of mature pre-ovulatory follicles on the day of hCG administration were similar to the primary efficacy results presented in Table 6 for the U.S. ART trial.

14.3 Induction of Spermatogenesis in Males

The efficacy of GONAL-f administered concomitantly with human chorionic gonadotropin (hCG) for induction of spermatogenesis in men with hypogonadotropic hypogonadism was established in three open-label, uncontrolled, non-randomized, multi-center, multi-national, escalating dose clinical trials (Trials 1, 2 and 3) conducted in 78 adult men (aged 16 to 48 years) with primary or secondary hypogonadotropic hypogonadism (defined as serum testosterone <100 ng/mL and low or normal FSH and LH) and azoospermia (sperm concentration <0.1×10^6/mL). Men were required at study entry to have normal serum cortisol and prolactin levels and be euthyroid. Men less than 21 years of age were required to have either confirmed anosmia or documented bone age >15 years to be eligible for study participation. Enrolled men received three to six months of pretreatment with hCG injection to normalize serum testosterone levels, followed by 18 months of treatment with GONAL-f and hCG.

Of the 78 men enrolled in the trials, 63 men were treated with GONAL-f and hCG.

Characteristics of the trial populations are shown in Table 7.

Table 7. Trial Population Characteristics in Trials 1, 2 and 3
 | Trial 1 N=32 | Trial 2 N=10 | Trial 3 N=36
Median age (range) (years) | 26 (16-48) | 37 (26-48) | 30 (20-44)
Race n(%)
Caucasian | 31 (97) | 7 (70) | 31 (86)
Asian | 1 (3) | 3 (30) | 3 (8)
African-American | 0 | 0 | 0
Other | 0 | 0 | 2 (6)
Prior treatment with gonadotropin (FSH) or GnRH [Gonadotropin releasing hormone (GnRH)] agonist [Prohibited in Trial 1] (%) | 0 | 5 (50) | 4 (11)
Mean (SD) testis volume (mL) [Mean testicular volume was required to be <4 mL in Trial 1 and <6 mL in Trial 3. Testicular size was not considered for enrollment into Trial 2.] | 2 (1) | 5 (3) | 4 (1)
N(%) with anosmia (i.e. diagnosis of Kallmann's syndrome) | 12 (37) | 2 (20) | 13 (36)

The primary efficacy measure in all trials was the proportion of men achieving a sperm density ≥ 1.5 × 10^6/mL during treatment with GONAL-f. Pregnancy (clinical and chemical) in partners of men desiring fertility was a secondary endpoint. Efficacy results in men who received at least one dose of GONAL-f and had at least one follow-up assessment are summarized in Table 8 and Table 9.

Table 8: Proportion of Men Receiving GONAL-f Who Achieved a Sperm Density ≥ 1.5 × 10^6/mL
 | Trial 1 (n=26) | Trial 2 (n=8) | Trial 3 (n=29)
Sperm Concentration ≥ 1.5 × 10^6/mL
Yes | 12 (46.2%) | 5 (62.5%) | 20 (80%)
No | 14 (53.8%) | 3 (37.5%) | 5 (20%)
Missing |  |  | 4
95% Confidence Interval | (26.6% - 66.6%) | (24.5% - 91.5%) | (40.7% - 82.8%)

Table 9: Pregnancy Outcome in Partners of Men Desiring Fertility
 | Trial 1 (n=7) [N reflects number of partners desiring pregnancy who had a partner at the time of enrollment, as not all enrolled men sought fertility] | Trial 2 (n=10) | Trial 3 (n=26),
Pregnancy | 6 (86%) | 3 (30%) | 5 (19%)
Pregnancy not reaching term | 1 (14%) | 1 (10%) | 2 (8%)
Single full-term live births | 5 (71%) | 2 (20%) | 3 (11%)

The time to achievement of sperm density ≥1.5 × 10^6/mL is summarized in Table 10.

Table 10: Time to Achievement of Sperm Density ≥ 1.5 × 10^6/ mL in Men Receiving GONAL-f
 | Trial 1 (n=26) | Trial 2 (n=8) | Trial 3 (n=29)
Number (%) of Men Achieving Sperm Concentration |  |  | 22 (76)
n | 12 (46) | 5 (62)
Time (Months) to Sperm Concentration ≥ 1.5 × 10^6/mL
Median | 12.4 | 9.1 | 9
Range | (2.7 – 18.1) | (8.8 – 11.7) | (2.8 – 18.2)

16 How Supplied/Storage and Handling

16.1 How Supplied

GONAL-f (follitropin alfa) for injection is supplied as a sterile, white lyophilized powder in multiple-dose vials of either 450 International Units per vial or 1050 International Units per vial.

The following package presentations are available:

NDC 44087-9030-1 - One multiple-dose vial of GONAL-f 450 International Units, one-1 mL prefilled diluent syringe of Bacteriostatic Water for Injection, USP (0.9% benzyl alcohol), and six administration syringes calibrated in FSH Units (IU FSH) with a fixed 27-gauge × 0.5-inch needle.

NDC 44087-9070-1 - One multiple-dose vial GONAL-f of 1050 International Units, one-2 mL prefilled diluent syringe of Bacteriostatic Water for Injection, USP (0.9% benzyl alcohol), and ten administration syringes calibrated in FSH Units (IU FSH) with a fixed 27-gauge × 0.5-inch needle.

16.2 Storage and Handling

Store vials refrigerated between 2°C to 8°C (36°F to 46°F) or at room temperature between 20°C to 25°C (68°F to 77°F).

Store reconstituted solution refrigerated between 2°C to 8°C (36°F to 46°F) or at room temperature between 20°C to 25°C (68°F to 77°F) and discard unused portion after 28 days. Protect from light [see Dosage and Administration (2.2)].

17 PATIENT COUNSELING INFORMATION

Advise women and men to read the FDA-approved patient labeling (Patient Information and Instructions for Use)

Hypersensitivity Reactions and Anaphylaxis

Advise women and men to discontinue GONAL-f and seek immediate medical attention if any signs or symptoms of a hypersensitivity reaction occur [see Warnings and Precautions (5.1)].

Ovarian Hyperstimulation Syndrome

Inform women regarding the risks of OHSS [see Warnings and Precautions (5.2] and OHSS-associated conditions including pulmonary and vascular complications [see Warnings and Precautions (5.3)] and ovarian torsion [see Warnings and Precautions (5.4)] with the use of GONAL-f. Advise women to seek medical attention if any of these conditions occur.

Abnormal Ovarian Enlargement

Inform women regarding the hazards associated with abnormal ovarian enlargement that may occur with GONAL-f therapy. If the ovaries are abnormally enlarged on the last day of GONAL-f therapy, inform women not to administer hCG and to avoid intercourse [see Warnings and Precautions (5.5)].

Multi-fetal Gestation and Birth

Advise the woman and her partner of the potential risk of multi-fetal gestation and birth before beginning therapy with GONAL-f [see Warnings and Precautions (5.6)].

Embryofetal Toxicity

Inform women that the incidence of congenital malformations (birth defects) after some Assisted Reproductive Technology [(ART) specifically in vitro fertilization (IVF) or intracytoplasmic sperm injection (ICSI)] may be slightly higher than after spontaneous conception [see Warnings and Precautions (5.7)].

Ectopic Pregnancy

Inform women undergoing ART that the incidence of ectopic pregnancy may be increased with these procedures, particularly for women with tubal abnormalities. Advise women who become pregnant and have: abdominal/pelvic pain (particularly on one side); shoulder, neck or rectal pain; and nausea and vomiting to seek immediate medical attention [see Warnings and Precautions (5.8)].

Spontaneous Abortion

Inform women that the risk of spontaneous abortion (miscarriage) is increased with gonadotropin products (including GONAL-f). However, causality has not been established. The increased risk may be a factor of the underlying infertility [see Warnings and Precautions (5.9)].

Lactation

Advise women not to breastfeed because the secretion of prolactin during lactation can result in inadequate response to ovarian stimulation with GONAL-f [see Use in Specific Populations (8.2)].

Dosing and Use of GONAL-f Multi Dose

Instruct women and men on the correct usage and dosing of GONAL-f [see Dosage and Administration (2.3, 2.4, 2.5)]. Caution against changing the dosage or the schedule of administration unless instructed to do so by a healthcare provider.

Duration and Necessary Monitoring in Patients Undergoing Therapy with GONAL-f

Prior to beginning therapy with GONAL-f, inform women and men about the time commitment and monitoring procedures necessary for treatment [see Dosage and Administration (2.3, 2.4, 2.5) and Warnings and Precautions (5.11)].

Instructions Regarding a Missed Dose

Inform women and men that if they miss or forget to take a dose of GONAL-f, they should not double the next dose and should call their healthcare provider for further dosing instructions.

Manufactured by:
EMD Serono, Inc.,
Boston, MA 02210 U.S.A.
US License No. 1773

Revised: 03/2025

PATIENT INFORMATION
GONAL-f® (gon-AL-eff)
(follitropin alfa) for injection
for subcutaneous use

What is GONAL-f?
GONAL-f is a prescription medicine containing follicle-stimulating hormone (FSH).
GONAL-f is used in:
infertile women to:

- help healthy ovaries develop (mature) and release an egg to help you get pregnant
- cause your ovaries to make multiple (more than 1) eggs as part of an Assisted Reproductive Technology (ART) program

infertile men to:

- help develop and produce mature sperm

Do not use GONAL-f if you are a woman or man who:

- is allergic to recombinant human FSH or any of the ingredients in GONAL-f. See the end of this leaflet for a complete list of ingredients in GONAL-f.
- has a high level of FSH in your blood that show your ovaries (women only) or testes (men only) do not work at all.
- has uncontrolled thyroid, adrenal, or pituitary problems.
- has a tumor in your sex organs (uterus, ovaries, or testes) or breasts.
- has a tumor in your brain, such as a tumor in your pituitary gland or hypothalamus.

Do not use GONAL-f if you are a woman that:

- has abnormal bleeding from your uterus or vagina from an unknown cause.
- has ovarian cysts or large ovaries from an unknown cause.

Before you start using GONAL-f, tell your healthcare provider about all of your medical conditions, including if you:

- have or have had asthma
- have been told by a healthcare provider that you have an increased risk for blood clots (thrombosis)
- have ever had a blood clot (thrombosis), or anyone in your family has ever had a blood clot (thrombosis)
- have had stomach (abdominal) surgery

Before you start using GONAL-f and are a woman, tell your healthcare provider if you:

- have had twisting of your ovary (ovarian torsion)
- had or have a cyst on your ovary
- have polycystic ovarian disease
- are pregnant or think you may be pregnant. GONAL-f is not for pregnant women. Your healthcare provider will give you a pregnancy test before you start using GONAL-f.
- are breastfeeding. It is not known if GONAL-f passes into your breast milk. You and your healthcare provider should decide if you will take GONAL-f or breastfeed. You should not do both.
- are not an adult. GONAL-f is not for children. It is not known if GONAL-f is safe or works in children.

Tell your healthcare provider about all the medicines you take, including prescription and over-the-counter medicines, vitamins, and herbal supplements.
Know the medicines you take. Keep a list of them to show your healthcare provider and pharmacist when you get a new medicine.

How should I use GONAL-f?

- Read the "Instructions for Use" that comes with GONAL-f for information about the right way to use GONAL-f.
- Use GONAL-f exactly as your healthcare provider tells you to.
- GONAL-f is given by injection under your skin. You can inject GONAL-f under the skin in your stomach (abdomen), upper arm, or upper leg.
- Do not inject GONAL-f at home until your healthcare provider has taught you the right way to inject it.
- Change your injection site as your healthcare provider showed you.
- Do not change your dose or the time you are scheduled to use GONAL-f unless your healthcare provider tells you to.
- If you miss or forget to take a dose, do not double your next dose. Ask your healthcare provider for instructions.
- Your healthcare provider will do blood and urine hormone tests while you are using GONAL-f. Make sure you follow-up with your healthcare provider to have your blood and urine tested when told to do so.
- Call your healthcare provider if you have any questions about your dose or how to use GONAL-f.

Women:

- Your healthcare provider may do ultrasound scans of your ovaries. Make sure you follow-up with your healthcare provider to have your ultrasound scans.

Men:

- Your healthcare provider may test your semen while you are using GONAL-f. Make sure you follow-up with your healthcare provider to give a semen sample for testing.

What are the possible side effects of GONAL-f?
GONAL-f may cause serious side effects in women and men, including:

- severe allergic reactions. Women or men who have used GONAL-f in the past may have a severe allergic reaction right away when they use GONAL-f again. This severe allergic reaction may lead to death. If you have any of the following symptoms of a severe allergic reaction, stop using GONAL-f and go to the nearest hospital emergency room right away:
  - shortness of breath
  - swelling of your face
  - itchy, red bumps or rash on your skin (hives)
- lung problems. GONAL-f may cause serious lung problems including fluid in your lungs (atelectasis), trouble breathing (acute respiratory distress syndrome), and worsening of asthma.
- blood clots. GONAL-f may increase your chance of having blood clots in your blood vessels. Blood clots can cause:
  - blood vessel problems (thrombophlebitis)
  - stroke
  - loss of your arm or leg
  - blood clot in your lung (pulmonary embolus)
  - heart attack

GONAL-f may cause serious side effects in women, including:

- ovarian hyperstimulation syndrome (OHSS). OHSS is both a serious and common side effect. Using GONAL-f may cause OHSS. OHSS is a serious medical condition that can happen when your ovaries produce too many eggs (overstimulated). OHSS can cause fluid to suddenly build up in the area of your stomach, chest, and heart, and can cause blood clots to form. In rare cases OHSS has caused death. OHSS may also happen after you stop using GONAL-f. Stop using GONAL-f and call your healthcare provider right away if you have symptoms of OHSS, including:

- trouble breathing
- nausea
- diarrhea

- severe lower stomach (pelvic) area pain
- vomiting
- decreased urine output

- weight gain

- twisting (torsion) of your ovary. GONAL-f may increase the chance of your ovary twisting if you already have certain conditions such as OHSS, pregnancy and previous abdominal surgery. Twisting of your ovary may lead to blood flow being cut off to your ovary.
- ovaries that are too large. GONAL-f may cause your ovaries to be abnormally large. Symptoms of large ovaries include bloating or pain in your lower stomach (pelvic) area.
- pregnancy with and birth of multiple babies. GONAL-f may increase your chance of having a pregnancy with more than 1 baby. Having a pregnancy and giving birth to more than 1 baby at a time increases the health risk for you and your babies. Your healthcare provider should tell you about your chances of multiple births.
- birth defects. A baby born after an ART cycle may have an increased chance of having birth defects. Your chances of having a baby with birth defects may increase depending on:
  - your age
  - certain sperm problems
  - your genetic background and that of your partner
  - a pregnancy with more than 1 baby at a time
- ectopic pregnancy (pregnancy outside your womb). GONAL-f may increase your chance of having a pregnancy that is abnormally outside of your womb. Your chance of having a pregnancy outside of your womb is increased if you also have fallopian tube problems. Call your healthcare provider right away if you have symptoms of an ectopic pregnancy including:

- stomach or pelvic pain especially on one side
- neck pain
- nausea and vomiting

- shoulder pain
- rectal pain

- miscarriage. Your chance of loss of an early pregnancy may be increased if you had difficulty becoming pregnant.
- tumors of the ovary. If you have used medicines like GONAL-f more than 1 time to get pregnant, you may have an increased chance of having tumors in your ovary(ies) (including cancer).

Common side effects of GONAL-f include:
in women:

- ovarian cyst
- OHSS
- pelvic pain
- gas

- headache
- stomach pain
- nausea
- bleeding between periods

in men:

- skin problems
- injection site pain
- tiredness

- breast enlargement
- seborrhea

Tell your healthcare provider if you have any side effect that bothers you or that does not go away. These are not all the possible side effects of GONAL-f. For more information, ask your healthcare provider or pharmacist.
Call your doctor for medical advice about side effects. You may report side effects to FDA at 1-800-FDA-1088.

How should I store GONAL-f?

- Before you use GONAL-f for the first time, store the vials:
  - in the refrigerator between 36°F to 46°F (2°C to 8°C) until the expiration date, or
  - store the vials at room temperature between 68°F to 77°F (20°C to 25°C) until the expiration date.
- After you use GONAL-f and there is still medicine left, store your vial in the refrigerator between 36°F to 46°F (2°C to 8°C) or at room temperature between 68°F to 77°F (20°C to 25°C) up to 28 days. Throw away any unused GONAL-f after 28 days.
- Store your GONAL-f vials in a safe place.
- Store GONAL-f away from light.

Keep GONAL-f and all medicines out of the reach of children.

General information about the safe and effective use of GONAL-f.
Medicines are sometimes prescribed for purposes other than those listed in a Patient Information leaflet. Do not use GONAL-f for a condition for which it was not prescribed. Do not give GONAL-f to other people, even if they have the same condition that you have. It may harm them.
You can ask your pharmacist or healthcare provider for information about GONAL-f that is written for health professionals.

For more information, go to www.fertilitylifelines.com, or call 1-866-538-7879.

What are the ingredients in GONAL-f?
Active ingredient: follitropin alfa (r-hFSH)
Inactive ingredients: dibasic sodium phosphate, monobasic sodium phosphate, phosphoric acid, sodium hydroxide, sucrose.
Manufactured by:
EMD Serono, Inc
Boston, MA 02210 USA
U.S. License 1773
EMD Serono, Inc. is an affiliate of Merck KGaA, Darmstadt, Germany

This Patient Package Insert has been approved by the U.S. Food and Drug Administration.

03/2025

Instructions for Use

GONAL-f®
(follitropin alfa) for injection
for subcutaneous use

Important

- Read these instructions completely before you begin.
- GONAL-f is for use under the skin only (subcutaneous).
- Only use GONAL-f if your healthcare provider trains you on how to use it correctly.

Warning:

- Do not reuse needles.
- Do not share your GONAL-f needles or syringes with another person. You may get a serious infection from other people or other people may get a serious infection from you.
- The syringes and needles that come with your GONAL-f are meant for use with GONAL-f only. Do not use GONAL-f syringes to inject other medicines or hormones.

Supplies needed to give your GONAL-f injection.

- a clean flat surface like a table
- 1 GONAL-f Multi-Dose vial
- 1 GONAL-f Multi-Dose Custom Dosing Injection Syringe
- 1 Prefilled Syringe of Bacteriostatic Water for Injection, USP
- 1 FDA-cleared sharps container
- 2 alcohol pads
- 1 gauze or cotton ball

Gather your supplies

- Prepare a clean, flat surface, such as a table or countertop, in a well-lit area.
- If the vial with the GONAL-f liquid mixed (reconstituted) solution is stored in the refrigerator, allow at least 30 minutes before you inject to let it warm to room temperature.

Caution: Do not use a microwave or other heating element to warm up the reconstituted liquid.

Step 1 Mixing (reconstituting)

- Wash your hands with soap and water.
- Using your thumb, flip off the plastic cap of the GONAL-f vial.
- Wipe the top of the vial stopper with an alcohol pad.
- Carefully twist and pull off the protective cap of the prefilled syringe of Bacteriostatic Water. Do not touch the needle or allow it to touch any surface.
- Hold the vial of GONAL-f powder firmly on a flat surface.
- Position the prefilled syringe of Bacteriostatic Water in a straight, upright position over the marked center circle of the rubber stopper on the vial of the GONAL-f powder.
- Insert the needle through the center circle of the rubber stopper on the vial of the GONAL-f powder while keeping it in a straight, upright position.
- Slowly inject the Bacteriostatic Water into the vial of GONAL-f powder by pressing down on the syringe plunger.
- Gently, rotate the vial between your fingers until the powder is dissolved. Do not shake.
- When all of the Bacteriostatic Water has been injected into the vial of GONAL-f powder, remove your finger from the syringe plunger and withdraw the needle from the vial. Immediately throw away (dispose of) the needle and syringe into your FDA-cleared sharps container (See Step 4: How to throw away used needles and syringes). Do not use this needle and syringe for your injection.

Step 2 Preparing the dose

- Check that the GONAL-f liquid solution is clear. Do not use if the liquid is discolored or contains any particles. If this happens, throw it away and call your healthcare provider or pharmacist right away.
- Allow the liquid solution to come to room temperature before giving your injection.
- Wipe the rubber stopper of the vial with an alcohol swab.
- Remove the wrapper and carefully, pull the needle cap off the Custom-Dosing Injection Syringe. Do not touch or allow the needle to touch any surface.
- Firmly hold the vial of GONAL-f liquid mixed (reconstituted) solution on a flat surface and insert the needle through the marked center circle of the rubber stopper.
- While keeping the needle in the vial, lift the vial and turn it upside down so that the needle points towards the ceiling.
- With the needle tip in the liquid, slowly pull back the plunger until the syringe fills to slightly more than the mark for your prescribed dose.
- Next, with the syringe pointing upward and keeping the needle in the vial, slowly push the syringe plunger to your prescribed dose and until all air bubbles are gone and a drop of liquid appears on the tip of the needle.
- Remove the syringe needle from the vial and recap the needle and set on a clean, flat surface.
- The syringe is now ready for giving your prescribed dose of GONAL-f.

Step 3 Injecting the dose

- Your healthcare provider should show you how to set the prescribed dose and use the syringe.
- Change your injection site each day to decrease discomfort. GONAL-f is injected under the skin (subcutaneously) of your stomach area, upper arm, or upper leg.
- Uncap the syringe and inject the prescribed dose as directed by your healthcare provider.
- Lightly press a cotton ball or gauze on the site if needed.

Step 4 How to throw away used needles and syringes

- Put used needles and syringes in an FDA-cleared sharps disposal container immediately after use.

Warning: Do not throw away loose needles in your household trash.

- If you do not have a FDA-cleared sharps disposal container, you may use a household container that is:
  - Made of heavy-duty plastic,
  - Can be closed with a tight-fitting, puncture-resistant lid, without sharps being able to come out,
  - Upright and stable during use,
  - Leak resistant, and
  - Properly labeled to warn of hazardous waste inside the container.
- When your sharps disposal container is almost full, you will need to follow your community guidelines for the right way to dispose of your sharps disposal container. There may be state or local laws about how you should throw away used needles and syringes. For more information about safe sharps disposal, and for specific information about sharps disposal in the state that you live in, go to the FDA's website at: http://www.fda.gov/safesharpsdisposal
  - Do not reuse the needles.
  - Do not throw way (dispose of) your used sharps disposal container in your household trash unless your community guidelines permit this.
  - Do not recycle your used sharps disposal container.

For more information, go to http:/www.fda.gov/safesharpsdisposal.

Step 5 How to store your GONAL-f vials

- Store all vials with GONAL-f away from light.
- Store vials in the refrigerator between 36° F and 46° F (2°C and 8° C) until the expiration date, or at room temperature between 68° F and 77° F (20°C and 25°C) until the expiration date.
- If you have medicine left in a vial after injecting, store it in the refrigerator or at room temperature for a maximum of 28 days from the day the powder was mixed with Bacteriostatic Water. After 28 days, you must throw away (discard) your vial with unused solution.
- Keep the GONAL-f vials and all medicines out of the reach of children.

Manufactured by:
EMD Serono, Inc
Boston, MA 02210 USA
US License No. 1773

EMD Serono, Inc. is an affiliate of Merck KGaA, Darmstadt, Germany

©2017 EMD Serono, Inc.

This Instructions for Use has been approved by the U.S. Food and Drug Administration. Revised 03/2025

PRINCIPAL DISPLAY PANEL - Kit Carton - 450 IU

NDC 44087-9030-1

GONAL-f®
(follitropin alfa) for injection
450 IU/vial

For subcutaneous injection
Rx only

1 Multiple-dose vial
1 pre-filled syringe of Bacteriostatic Water
for Injection, USP (0.9% benzyl alcohol)
6 administration syringes with fixed needle
(27-gauge)

EMD
SERONO

PRINCIPAL DISPLAY PANEL - Kit Carton - 1050 IU

NDC 44087-9070-1

GONAL-f®
(follitropin alfa) for injection
1050 IU/vial

For subcutaneous injection
Rx only

1 Multiple-dose vial
1 pre-filled syringe of Bacteriostatic Water
for Injection, USP (0.9% benzyl alcohol)
10 administration syringes with fixed needle
(27-gauge)

EMD
SERONO